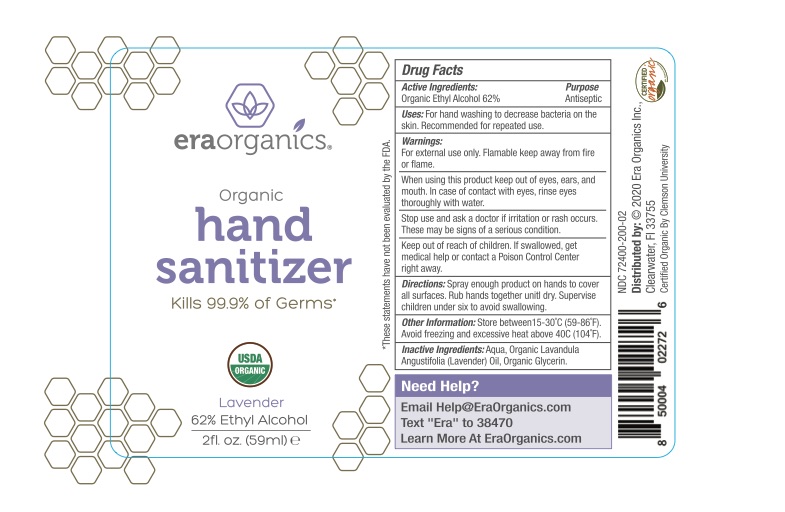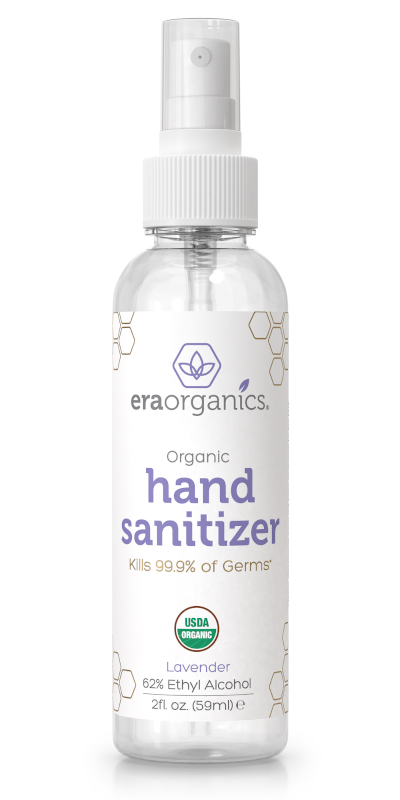 DRUG LABEL: Organic Hand Sanitizer Lavender
NDC: 72400-200 | Form: SPRAY
Manufacturer: Era Organics
Category: otc | Type: HUMAN OTC DRUG LABEL
Date: 20200618

ACTIVE INGREDIENTS: ALCOHOL 36.58 mL/59 mL
INACTIVE INGREDIENTS: WATER; LAVENDER OIL; GLYCERIN

Era Organics Organic Lavender Hand Sanitizer Spray 2oz

Active Ingredients

Organic Ethyl Alcohol 62%

Purpose

Antiseptic

Uses

For hand washing to decrease bacteria on the skin. Recommended for repeated use.

Warnings

For external use only. Flammable keep away from fire or flame.

When using this product keep out of eyes, ears and mouth. In case of contact with eyes, rinse eyes thoroughly with water.

Stop use and ask a doctor if irritation or rash occurs. These may be signs of a serious condition.

Keep out of reach of children. If swallowed, get medical help or contact a Poison Control Center right away.

Directions

Spray enough product on hands to cover all surfaces. Rub hands together until dry. Supervise children under six to avoid swallowing.

Other Information

Store between 15-30 C (59-86F).

Avoid freezing and excessive heat above 40C (104F).

Inactive Ingredients

Aqua, Organics Lavandula Angustifolia (Lavender) Oil, Organic Glycerin.

Need Help?

Email Help@EraOrganics.com

Text "Era" to 38470

Learn More At EraOrganics.com

2oz packaging and label

2FL OZ NDC: 72400-200-02